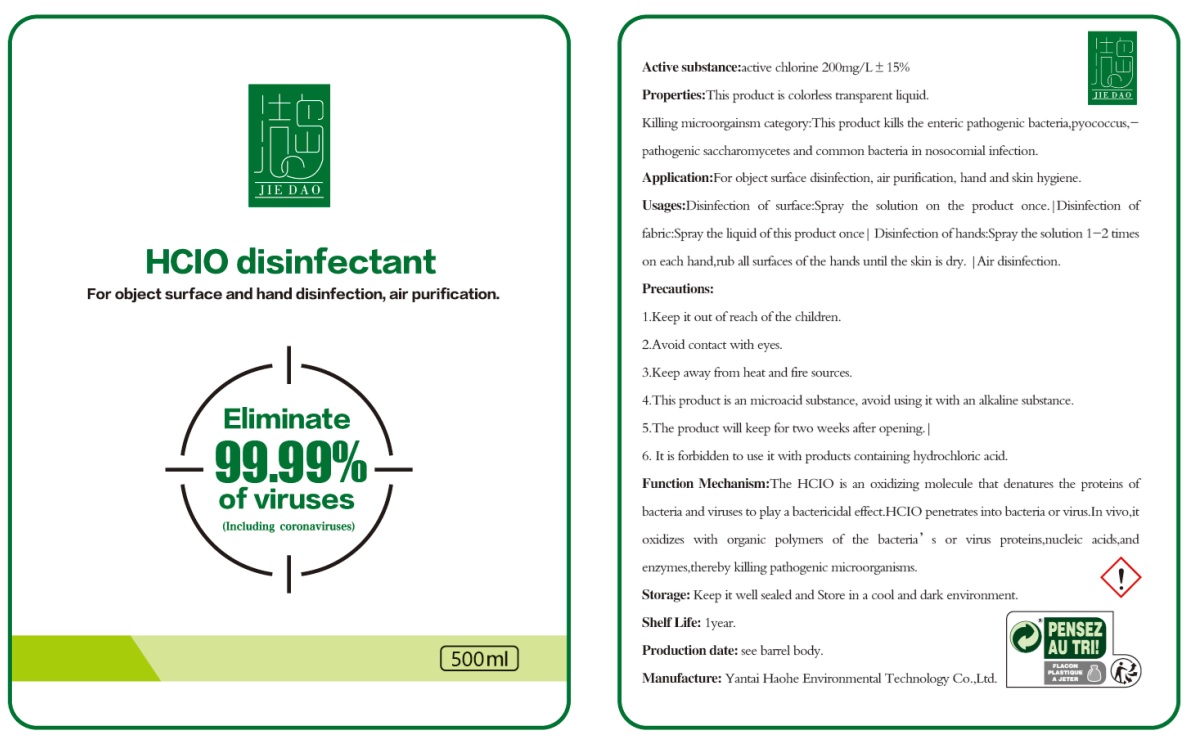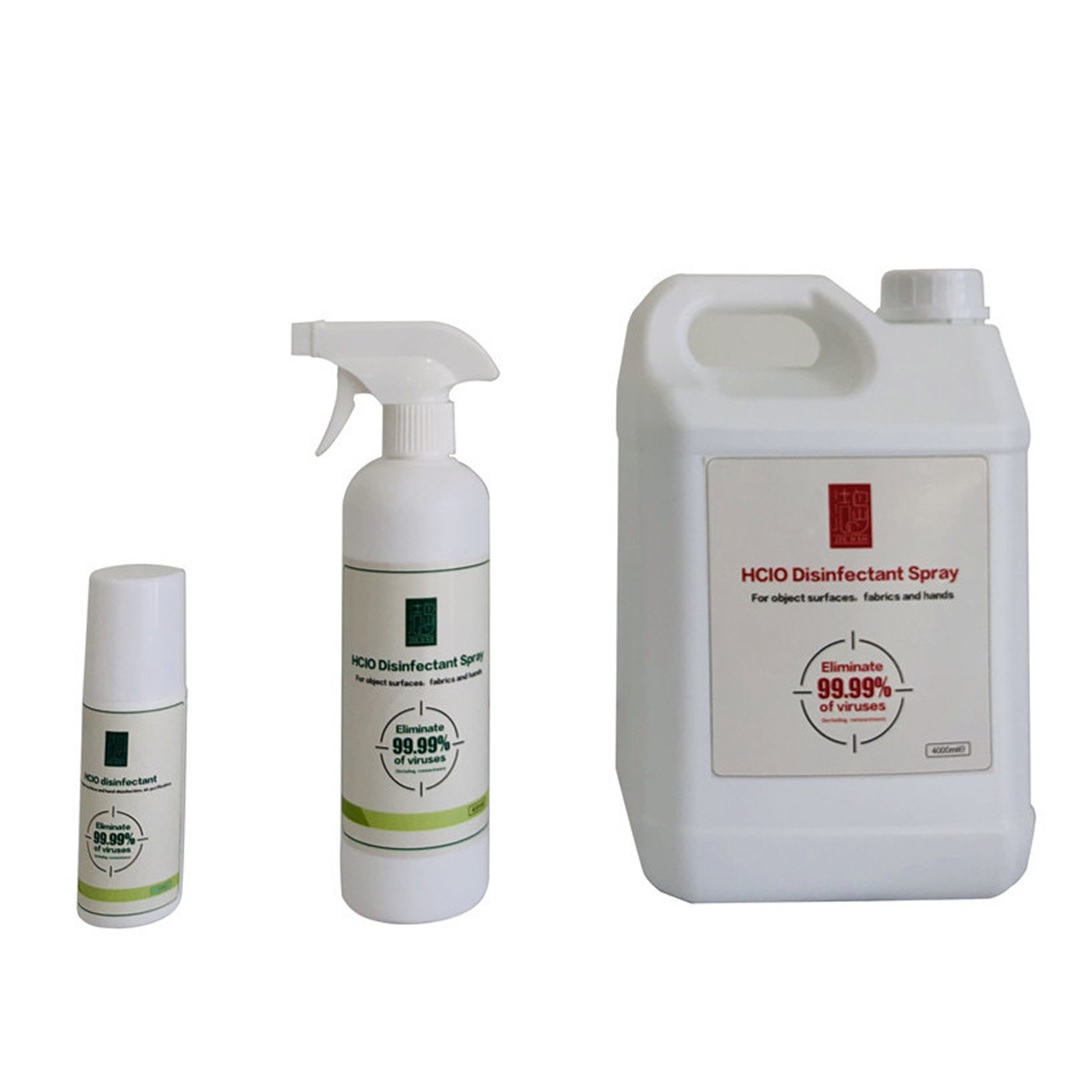 DRUG LABEL: HCIO disnfectant
NDC: 90068-101 | Form: LIQUID
Manufacturer: Shandong Longhe Energy-saving Technology Co., Ltd.
Category: otc | Type: HUMAN OTC DRUG LABEL
Date: 20200803

ACTIVE INGREDIENTS: HYPOCHLOROUS ACID 0.2 mg/1 mL
INACTIVE INGREDIENTS: WATER

HCIO disnfectant

HCIO disnfectant

Active Ingredient(s)

HYPOCHLOROUS ACID 0.1mg/mL. Purpose: Antiseptic

Purpose

Antiseptic, HCIO disnfectant

Use

HCIO disnfectant to help reduce bacteria that potentially can cause disease.

Warnings

For external use only. Flammable. Keep away from heat or flame

Do not use

- in children less than 2 months of age
- on open skin wounds

When using this product keep out of eyes, ears, and mouth. In case of contact with eyes, rinse eyes thoroughly with water.
Stop use and ask a doctor if irritation or rash occurs. These may be signs of a serious condition.
Keep out of reach of children. If swallowed, get medical help or contact a Poison Control Center right away.

Stop use and ask a doctor if irritation or rash occurs. These may be signs of a serious condition.

Keep out of reach of children. If swallowed, get medical help or contact a Poison Control Center right away.

Directions

- Spray the solution 1-2 times on each hand, rub all surfaces of the hands until the skin is dry.
- Supervise children under 6 years of age when using this product to avoid swallowing.

Other information

- Store between 15-30C (59-86F)
- Avoid freezing and excessive heat above 40C (104F)

Inactive ingredients

purified water USP